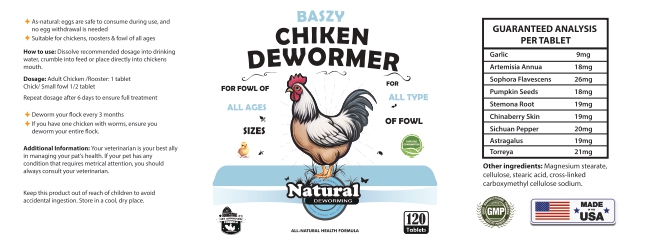 DRUG LABEL: Chicken Dewormer
NDC: 86202-0250 | Form: TABLET
Manufacturer: AMBIENCE FAMILY INC
Category: animal | Type: OTC ANIMAL DRUG LABEL
Date: 20240818

ACTIVE INGREDIENTS: GARLIC 9 mg/270 mg; ARTEMISIA ANNUA POLLEN 18 mg/270 mg; SOPHORA FLAVESCENS ROOT 26 mg/270 mg
INACTIVE INGREDIENTS: PUMPKIN SEED 18 mg/270 mg; STEMONA JAPONICA ROOT 19 mg/270 mg; PEPPERS 20 mg/270 mg; TORREYA GRANDIS SEED 21 mg/270 mg

BASZY Chicken Dewormer

WARNINGS AND PRECAUTIONS

no egg withdrawal is needed. Suitable for chickens, roosters & fowl of all ages
water, crumble into feed or place directly into chickens mouth,
Repeat dosage after 6 days to ensure full treatment
Deworm your flock every 3 months + If you have one chicken with worms, ensure you deworm your entire
flockAdditional Information: Your veterinarian is your best ally inmanaging your pat's health. If your pet has
any condition that requires metrical attention, you should always consult your veterinarian.
Keep this product out of reach of children to avoid accidental ingestion. Store in a cool, dry place

WARNINGS AND PRECAUTIONS

Not for use in humans. Keep out of reach of children. Protective gloves should be used and care should be taken
when handling the product to avoid skin and eye exposure and accidental ingestion. Accidental exposure may result
in skin and eye irritation. Accidental ingestion may cause gastrointestinal disturbances and hypersensitivity reactions
in humans.

PACKAGE LABEL

no egg withdrawal is needed Suitable for chickens, roosters & fowl of all ages
water, crumble into feed or place directly into chickens mouth,
Repeat dosage after 6 days to ensure full treatment
Deworm your flock every 3 months + If you have one chicken with worms, ensure you deworm your entire
flockAdditional Information: Your veterinarian is your best ally inmanaging your pat's health. If your pet has
Not for use in humans. Keep out of reach of children. Protective gloves should be used and care should be taken
when handling the product to avoid skin and eye exposure and accidental ingestion. Accidental exposure may result
in skin and eye irritation. Accidental ingestion may cause gastrointestinal disturbances and hypersensitivity reactions
in humans.
any condition that requires metrical attention, you should always consult your veterinarian.
Keep this product out of reach of children to avoid accidental ingestion. Store in a cool, dry place.

GUARANTEED ANALYSIS
PER TABLET
Garlic 9mg
‘Artemisia Annua 18mg
Sophora Flavescens 26mg
Pumpkin Seeds 18mg
‘Stemona Root 19mg
Chinaberry Skin 19mg
Sichuan Pepper 20mg
Astragalus 19mg
Torreya 21mg
Other ingredients: Magnesium stearate,
cellulose, st i, cross-linked carboxymethyl cellulose sodium.

Content of labling